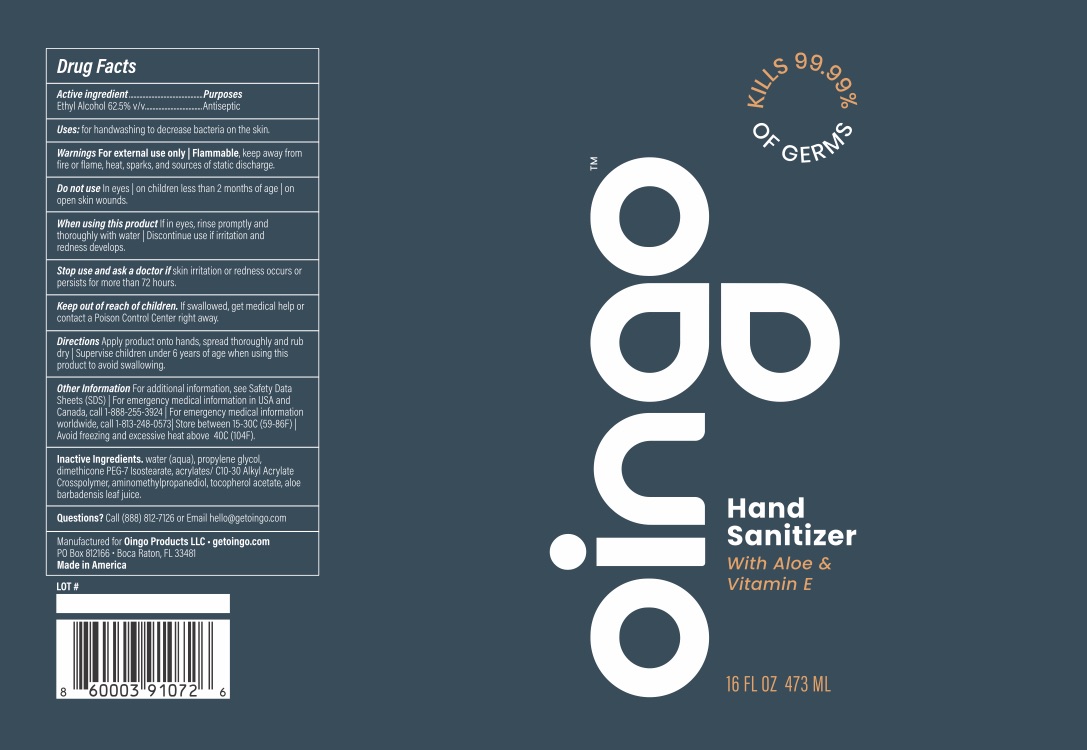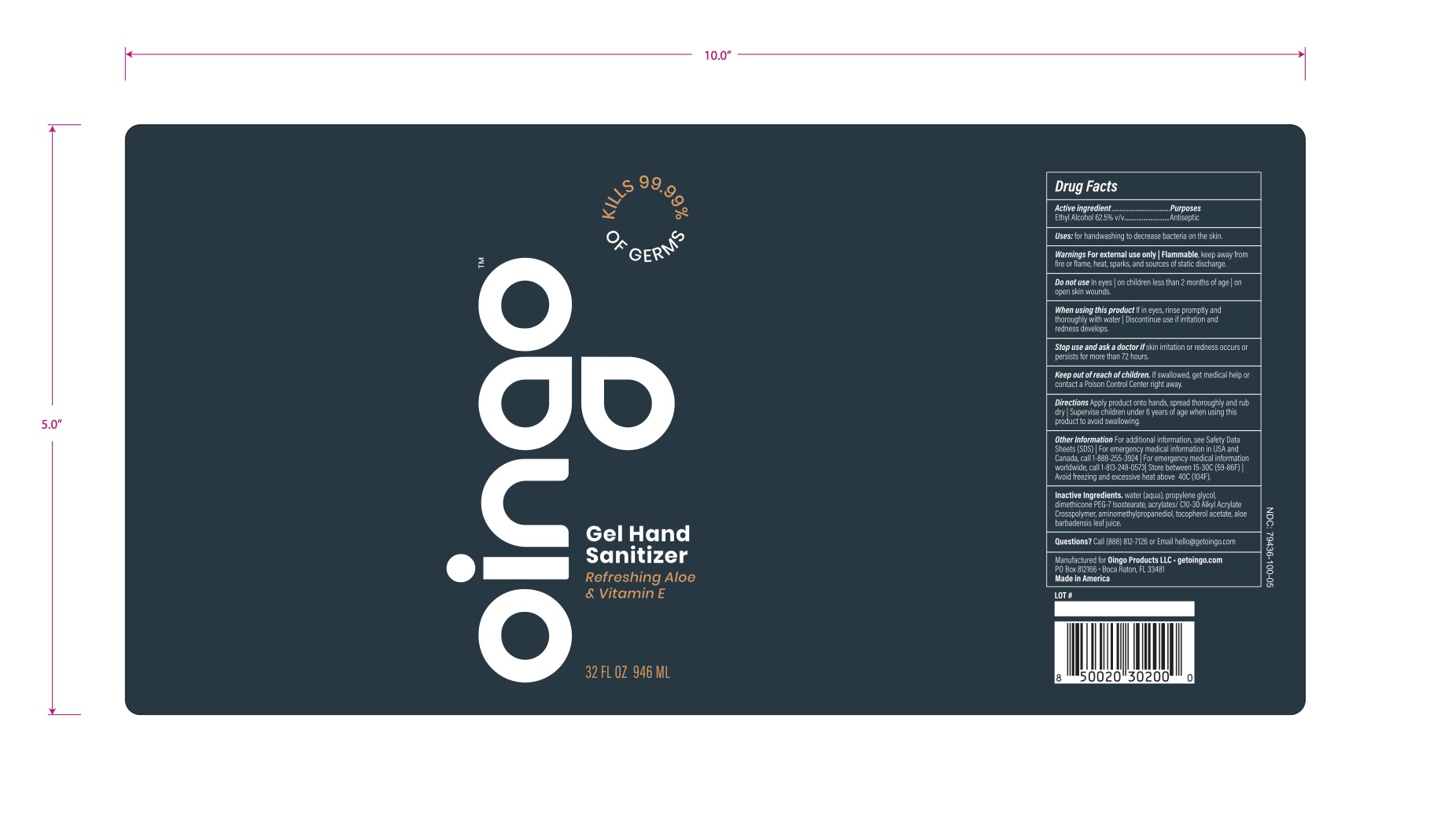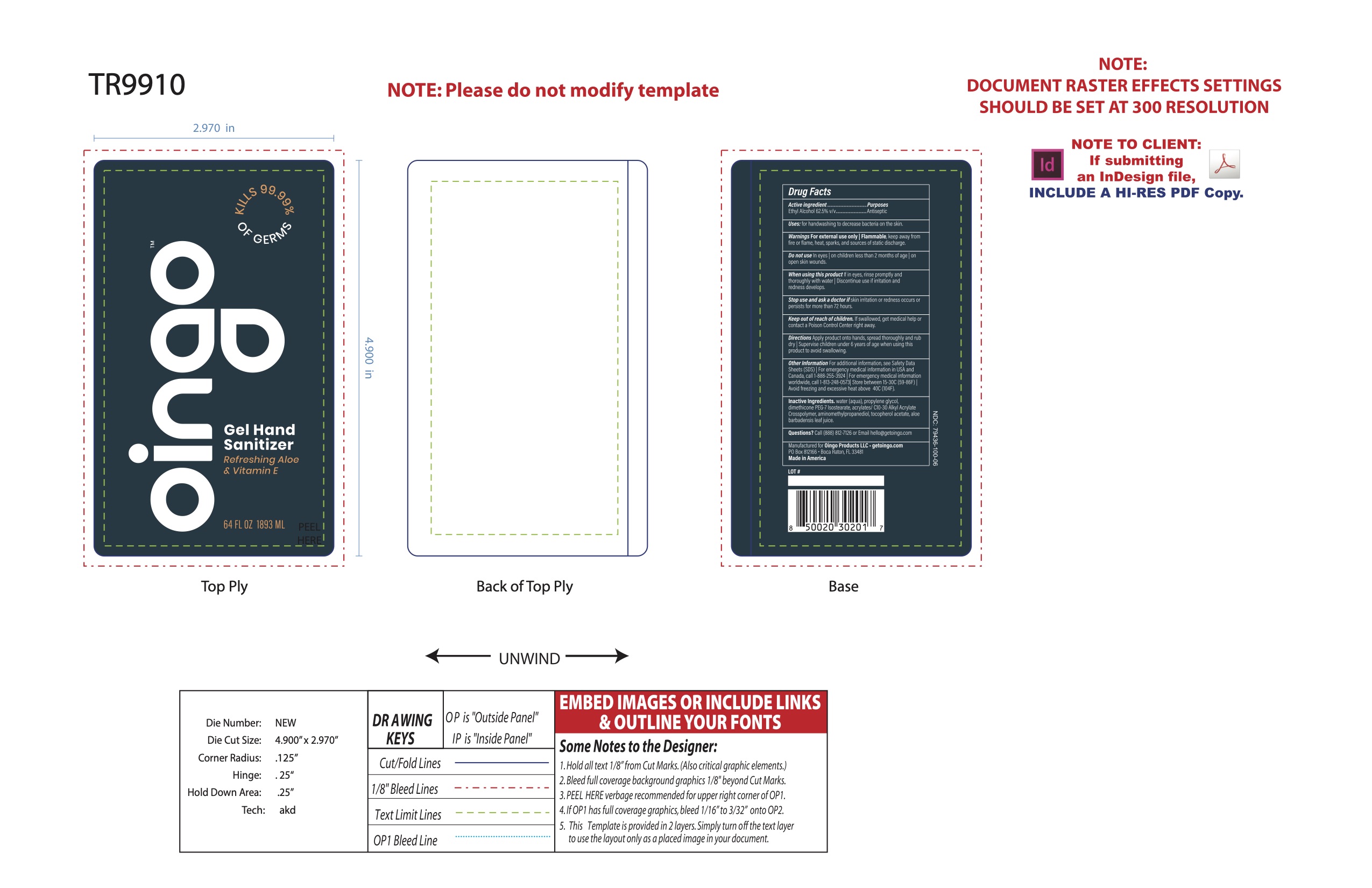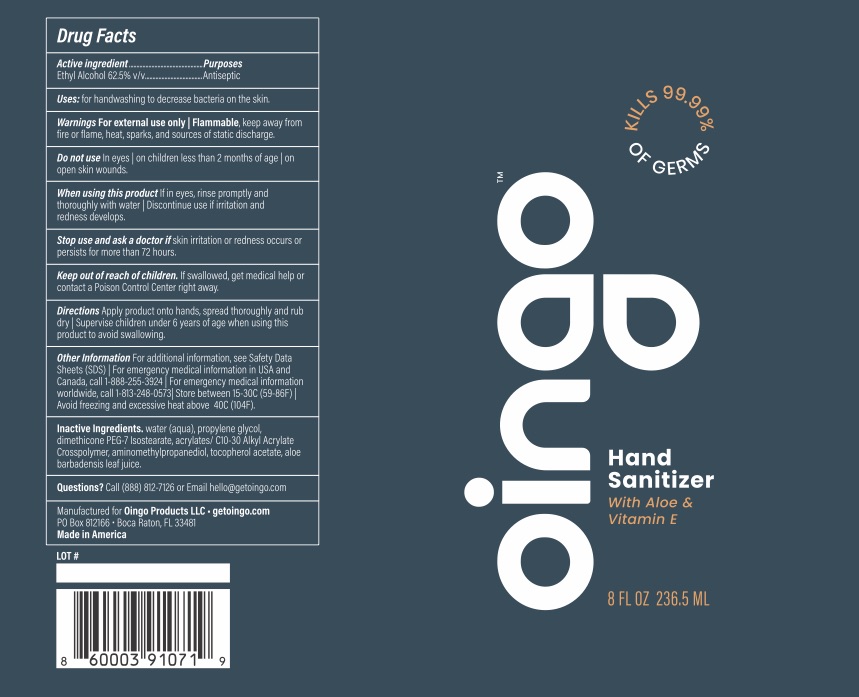 DRUG LABEL: Hand Sanitizer
NDC: 79436-101 | Form: GEL
Manufacturer: Oingo Products LLC
Category: otc | Type: HUMAN OTC DRUG LABEL
Date: 20200818

ACTIVE INGREDIENTS: ALCOHOL 65 mL/100 mL
INACTIVE INGREDIENTS: WATER; ALOE; AMINOMETHYL PROPANEDIOL; PPG-14 BUTYL ETHER; .ALPHA.-TOCOPHEROL ACETATE, D-; CARBOMER INTERPOLYMER TYPE A (55000 CPS); DIMETHICONE PEG-7 ISOSTEARATE

Active Ingredient(s)

Ethyl Alcohol 62.5% v/v…………………..……... Antiseptic

Use

Hand Sanitizer to help reduce bacteria that potentially can cause disease. For use when soap and water are not available.

Warnings

For external use only | Flammable, keep away from fire or flame, heat, sparks, and sources of static discharge

Do not use

In eyes | on children less than 2 months of age | on open skin wounds

When Using

If in eyes, rinse promptly and thoroughly with water | Discontinue use if irritation and redness Develops

Stop use and ask a doctor

if skin irritation or redness occurs

or persists for more than 72 hours.

Keep out of reach of children.

If swallowed, get medical help

or contact a Poison Control Center right away.

Directions

Apply product onto hands, spread thoroughly and

rub dry | Supervise children under 6 years of age when using

this product to avoid swallowing.

Other information

Other Information For additional information, see Safety Data

Sheets (SDS) | For emergency medical information in USA and

Canada, call 1-888-255-3924 | Store between 15-

30C (59-86F) | Avoid freexing and excessive heat above 40C

(104F)

Inactive ingredients

water (aqua), propylene glycol,

dimethicone PEG-7 Isostearate, acrylates/ C10-30 Alkyl

Acrylate Crosspolymer, aminomethylpropanediol, tocopherol

acetate, aloe barbadensis leaf juice

Purpose

Antiseptic, Hand Sanitizer

Package Label - Principal Display Panel

236.5 mL NDC: 79436-101-03

473 mL NDC: 79436-101-04